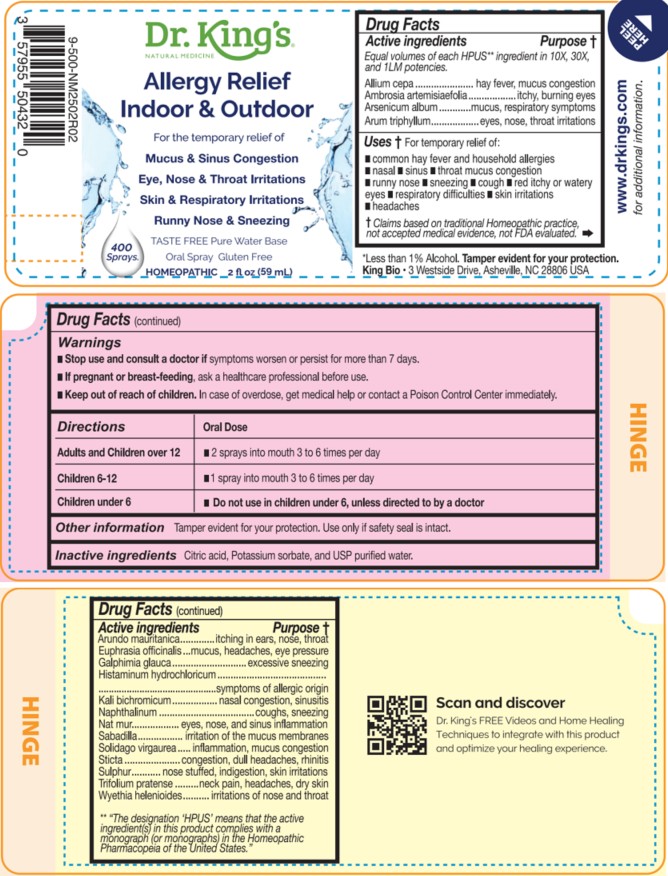 DRUG LABEL: Allergy Relief Indoor and Outdoor
NDC: 57955-9997 | Form: LIQUID
Manufacturer: King Bio Inc.
Category: homeopathic | Type: HUMAN OTC DRUG LABEL
Date: 20260302

ACTIVE INGREDIENTS: ONION 10 [hp_X]/59 mL; AMBROSIA ARTEMISIIFOLIA WHOLE 10 [hp_X]/59 mL; ARSENIC TRIOXIDE 10 [hp_X]/59 mL; ARISAEMA TRIPHYLLUM ROOT 10 [hp_X]/59 mL; ARUNDO PLINIANA ROOT 10 [hp_X]/59 mL; EUPHRASIA STRICTA 10 [hp_X]/59 mL; GALPHIMIA GLAUCA FLOWERING TOP 10 [hp_X]/59 mL; HISTAMINE DIHYDROCHLORIDE 10 [hp_X]/59 mL; POTASSIUM DICHROMATE 10 [hp_X]/59 mL; NAPHTHALENE 10 [hp_X]/59 mL; SODIUM CHLORIDE 10 [hp_X]/59 mL; SCHOENOCAULON OFFICINALE SEED 10 [hp_X]/59 mL; SOLIDAGO VIRGAUREA FLOWERING TOP 10 [hp_X]/59 mL; LOBARIA PULMONARIA 10 [hp_X]/59 mL; SULFUR 10 [hp_X]/59 mL; TRIFOLIUM PRATENSE FLOWER 10 [hp_X]/59 mL; WYETHIA HELENIOIDES ROOT 10 [hp_X]/59 mL
INACTIVE INGREDIENTS: ANHYDROUS CITRIC ACID; POTASSIUM SORBATE; WATER

Allergy Relief Indoor and Outdoor

Active ingredients

Equal volumes of each HPUS** ingredient in 10X,
30X, and 1LM potencies.

Allium cepa, Ambrosia artemisiaefolia, Arsenicum album, Arum triphyllum, Arundo mauritanica, Euphrasia officinalis, Galphimia glauca, Histaminum hydrochloricum, Kali bichromicum, Naphthalinum, Natrum muriaticum, Sabadilla, Solidago virgaurea, Sticta pulmonaria, Sulphur, Trifolium pratense, and Wyethia helenioides.

** "The designation 'HPUS’ means that the active ingredient(s) in this product complies with a monograph (or Monographs) in the Homeopathic Pharmacopeia of the United States.″

INDICATIONS AND USAGE

Uses † for temporary relief of:

- common hay fever and household allergies
- nasal
- sinus
- throat mucus congestion
- runny nose
- sneezing
- cough
- red itchy or watery eyes
- respiratory difficulties
- skin irritations
- headaches

† Claims based on traditional Homeopathic practice, not accepted medical evidence, not
FDA evaluated.

QUESTIONS

Allergy Relief Indoor & Outdoor

TASTE FREE Pure Water Base

Oral Spray Gluten Free

Less than 1% Alcohol Tamper evident for your protection.

King Bio, Inc. 3 Westside Drive

Asheville, NC 28806 USA

For latest product information and instructions: www.DrKings.com

Scan and discover Dr. King's FREE Videos and Home Healing
Techniques to integrate with this product and optimize your healing experience.

Warnings

- Stop use and consult a doctor if symptoms worsen or persist for more than 7 days.

- If pregnant or breast-feeding, ask a healthcare professional before use.

- Keep out of reach of children. In case of overdose, get medical help or contact a Poison Control Center immediately.

Directions

Directions | Oral Dose
Adults and Children over 12 | - 2 sprays into mouth 3 to 6 times per day
Children 6-12 | - 1 spray into mouth 3 to 6 times per day
Children under 6 | - Do not use in children under 6, unless directed to by a doctor

Other information

Tamper evident for your protection.

Use only if safety seal is intact.

Inactive Ingredients

Citric acid, Potassium sorbate, and USP purified water.

Drug Facts

Active ingredients Purpose †

Equal volumes of each HPUS** ingredient in 10X, 30X, and 1LM potencies.

Allium cepa ...............................................hay fever, mucus congestion
Ambrosia artemisiaefolia ..........................................itchy, burning eyes
Arsenicum album......................................mucus, respiratory symptoms
Arum triphyllum ..........................................eyes, nose, throat irritation

Arundo muritanica........................................itching in ears, nose, throat
Euphrasia officinalis ..............................mucus, headaches, eye pressure
Galphimia glauca .....................................................excessive sneezing
Histaminum hydrocholoricum..........................symptoms of allergic origin
Kali bichromicum............................................nasal congestion, sinusitis
Naphthalinum.............................................................coughs, sneezing
Natrum muriaticum.............................eyes, nose, and sinus inflammation
Sabadilla............................................irritation of the mucus membranes
Solidago virgaurea .................................inflammation, mucus congestion
Sticta pulmonaria ...............................congestion, dull headaches, rhinitis
Sulphur ......................................nose stuffed, indigestion, skin irritations
Trifolium pratense .....................................neck pain, headaches, dry skin
Wyethia helenioides......................................irritations of nose and throat

** "The designation 'HPUS’ means that the active ingredient(s) in this product complies with a monograph (or Monographs) in the Homeopathic Pharmacopeia of the United States.″

† Claims based on traditional Homeopathic practice, not accepted medical evidence, not FDA evaluated.